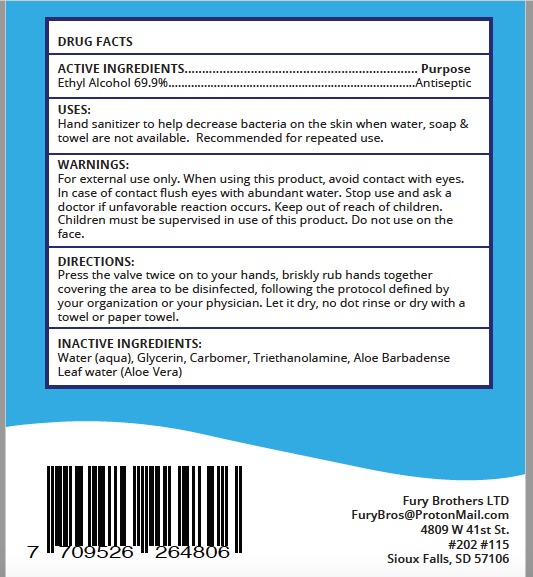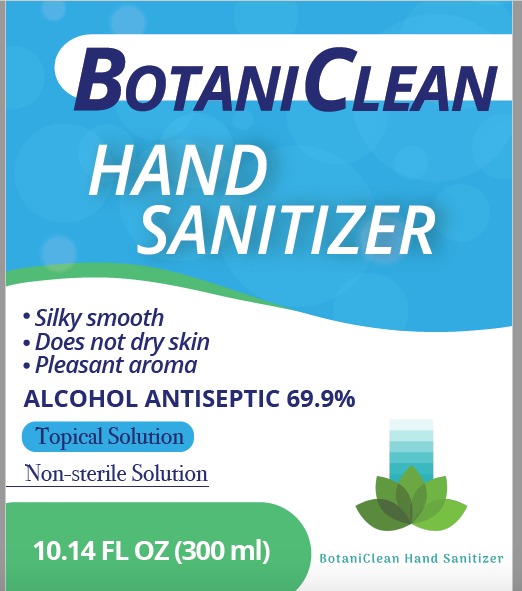 DRUG LABEL: BotaniClean
NDC: 78934-319 | Form: LIQUID
Manufacturer: LYR FARMACEUTICA LTDA
Category: otc | Type: HUMAN OTC DRUG LABEL
Date: 20200609

ACTIVE INGREDIENTS: ALCOHOL 69.9 mL/100 mL
INACTIVE INGREDIENTS: GLYCERIN 8 mL/100 mL; TROLAMINE 1 mL/100 mL; ALOE VERA LEAF 7 mL/100 mL; WATER 13.1 mL/100 mL; CARBOMER HOMOPOLYMER, UNSPECIFIED TYPE 1 mL/100 mL

Hand Sanitizer

Active Ingredients

Ethyl Alcohol 69.9%

Purpose

Antiseptic

USES

Hand sanitizer to help decrease bacteria on the skin when water, soap & towels are not available. Recommended for repeated use.

WARNINGS

For external use only.

When using this product, avoid contact with eyes. In case of contact flush eyes with abundant water.

Stop use and ask a doctor if unfavorable reaction occurs.

Keep out of reach of children. children must be supervised in use of this product.

Do not use on the face.

DIRECTIONS

Press the valve twice on to your hands, briskly rub hands together covering the area to be disinfected, following the protocol defined by your organization or your physician. Let it dry, do not rinse or dry with a towel or paper towel.

INACTIVE INGREDIENTS

Water (aqua), Glycerin, Carbomer, Triethanolamine, Aloe Barbadense Leaf
Water (Aloe Vera)

PACKAGE LABEL

300 mL NDC: 78934-319-03